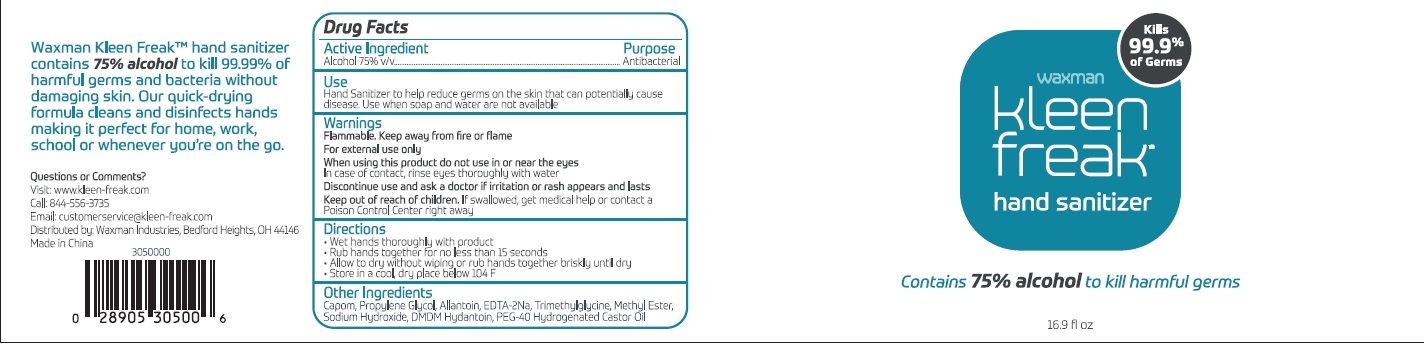 DRUG LABEL: Kleen Freak hand sanitizer
NDC: 74447-106 | Form: LIQUID
Manufacturer: Guangzhou Minghui Cosmetics Co., Ltd.
Category: otc | Type: HUMAN OTC DRUG LABEL
Date: 20200718

ACTIVE INGREDIENTS: ALCOHOL 75 mL/100 mL
INACTIVE INGREDIENTS: PROPYLENE GLYCOL; ALLANTOIN; BETAINE; METHYL 2-FUROATE; SODIUM HYDROXIDE; DMDM HYDANTOIN; POLYOXYL 40 HYDROGENATED CASTOR OIL

Active ingredient

Alcohol 75% (V/V)

Purpose

Antibacterial

Use

Hand sanitizer to help reduce germs on the skin that an potntially cause disease. Use when soap and water are not available

Warnings

For external use only.

Flammable,

Keep away from fire or flame

When using this product do not use in or near the eyes

In case of contact, rinse eyes thoroughly with water.

Discontinue use and ask a doctor if

irritation or rash appears and lasts.

Keep out of reach of children.

If swallowed, get medical help or contact a Poison Control Center right away.

Directions

- Wet hands thoroughly with product.
- Rub hands together for no less than 15 seconds
- Allow to dry without wiping or rub hands together briskly until dry
- Store in a cool dry place below 104℉

Inactive ingredients

Capom, Propylene Glycol, Allantoin, EDTA-2Na, Trimethylglycine, Methyl ESter, Sodium Hydroxide, DMDM Hydantoin, PEG-40 Hydrogenated Castor Oil